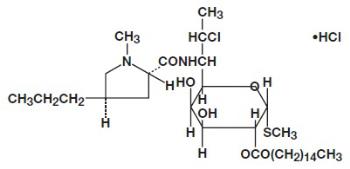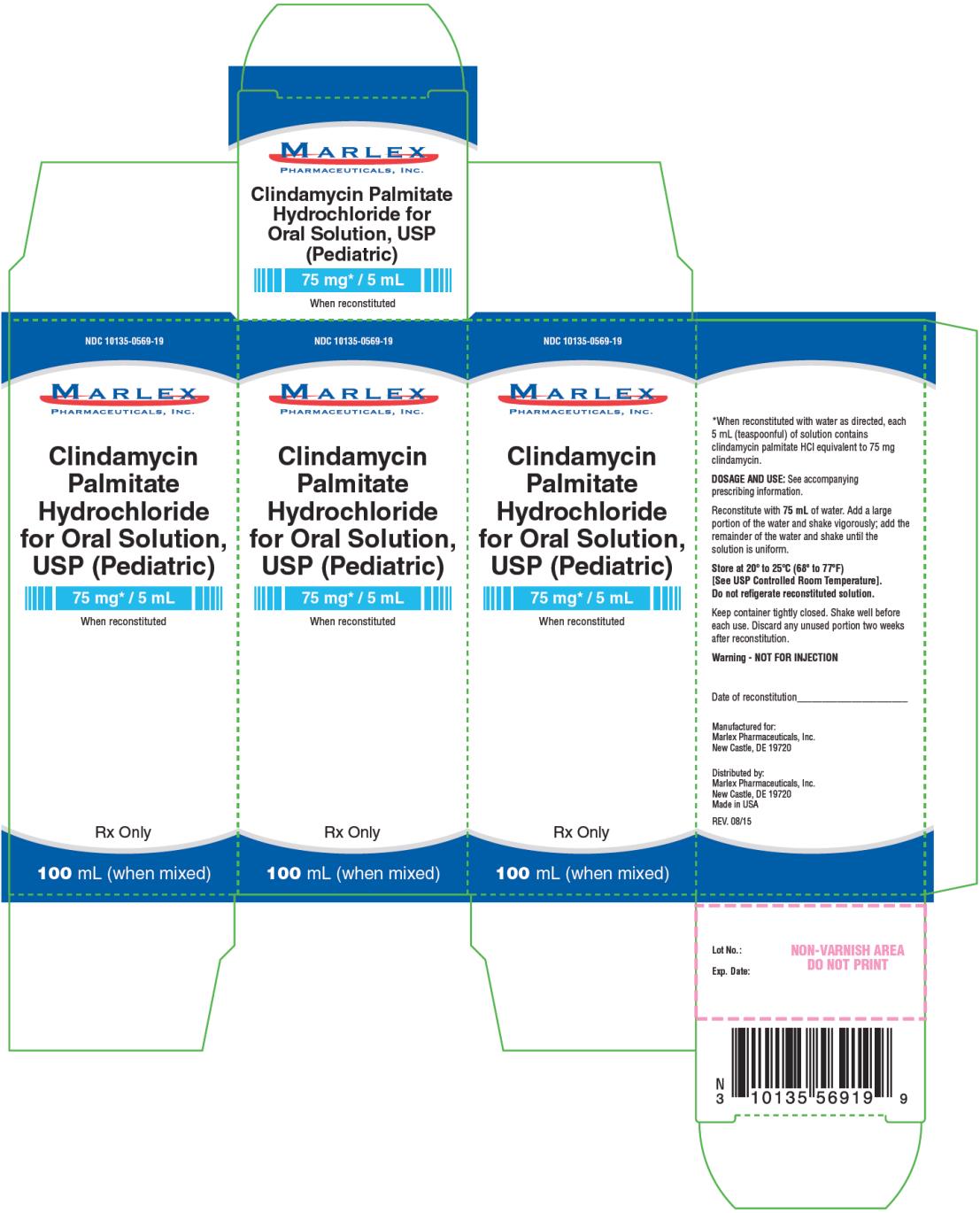 DRUG LABEL: Clindamycin Palmitate Hydrochloride
NDC: 10135-569 | Form: SOLUTION
Manufacturer: Marlex Pharmaceuticals Inc
Category: prescription | Type: HUMAN PRESCRIPTION DRUG LABEL
Date: 20191018

ACTIVE INGREDIENTS: CLINDAMYCIN PALMITATE HYDROCHLORIDE 75 mg/5 mL
INACTIVE INGREDIENTS: ICODEXTRIN; ETHYLPARABEN; POLOXAMER 188; SUCROSE

Clindamycin Palmitate Hydrochloride

CLINDAMYCIN PALMITATE HYDROCHLORIDE- clindamycin palmitate
hydrochloride powder, for solution
Marlex Pharmaceuticals Inc. of New Castle, Delaware

----------

Clindamycin Palmitate Hydrochloride for Oral Solution, USP (Pediatric)

To reduce the development of drug-resistant bacteria and maintain the effectiveness of clindamycin palmitate hydrochloride (HCl) for oral solution, USP (pediatric) and other antibacterial drugs, clindamycin palmitate HCl for oral solution, USP (pediatric) should be used only to treat or prevent infections that are proven or strongly suspected to be caused by bacteria.

Not for Injection

WARNING

Clostridium difficile associated diarrhea (CDAD) has been reported with use of nearly all antibacterial agents, including clindamycin and may range in severity from mild diarrhea to fatal colitis. Treatment with antibacterial agents alters the normal flora of the colon leading to overgrowth of C.difficile.

Because clindamycin therapy has been associated with severe colitis which may end fatally, it should be reserved for serious infections where less toxic antimicrobial agents are inappropriate, as described in the INDICATIONS AND USAGE section. It should not be used in patients with nonbacterial infections such as most upper respiratory tract infections.

C.difficile produces toxins A and B which contribute to the development of CDAD. Hypertoxin producing strains of C.difficile cause increased morbidity and mortality, as these infections can be refractory to antimicrobial therapy and may require colectomy. CDAD must be considered in all patients who present with diarrhea following antibiotic use. Careful medical history is necessary since CDAD has been reported to occur over two months after the administration of antibacterial agents. If CDAD is suspected or confirmed, ongoing antibiotic use not directed against C.difficile may need to be discontinued. Appropriate fluid and electrolyte management, protein supplementation, antibiotic treatment of C.difficile, and surgical evaluation should be instituted as clinically indicated.

DESCRIPTION

Clindamycin palmitate hydrochloride is a water soluble hydrochloride salt of the ester of clindamycin and palmitic acid. Clindamycin is a semisynthetic antibiotic produced by a 7(S)-chloro-substitution of the 7(R)-hydroxyl group of the parent compound lincomycin.

The structural formula is represented below:

The chemical name for clindamycin palmitate hydrochloride is Methyl 7-chloro-6, 7, 8-trideoxy-6-(1-methyl-trans-4propyl-L-2-pyrrolidinecarboxamido)-1-threo-a-D-galacto-octopyranoside 2-palmitate monohydrochloride. Clindamycin palmitate HCl for oral solution, USP (pediatric) contains clindamycin palmitate hydrochloride granules for reconstitution. Each 5 mL contains the equivalent of 75 mg clindamycin.

Inactive ingredients: artificial cherry flavor, dextrin, ethylparaben, poloxamer 188, sucrose.

CLINICAL PHARMACOLOGY

Microbiology

Although clindamycin palmitate HCl is inactive in vitro, rapid in vivo hydrolysis converts this compound to the antibacterially active clindamycin.

Clindamycin has been shown to have in vitro activity against isolates of the following organisms:

Aerobic gram positive cocci, including:

•Staphylococcus aureus (penicillinase and non-penicillinase producing strains). When tested by in vitro methods some staphylococcal strains originally resistant to erythromycin rapidly develop resistance to clindamycin.

•Staphylococcus epidermidis (penicillinase and non-penicillinase producing strains). When tested by in vitro methods some staphylococcal strains originally resistant to erythromycin rapidly develop resistance to clindamycin.

•Streptococci (except Streptococcus faecalis)

•Pneumococci

Anaerobic gram negative bacilli, including:

•Bacteroides species (including Bacteroides fragilis group and Bacteroides melaninogenicus group)

•Fusobacterium species

Anaerobic gram positive nonsporeforming bacilli, including:

•Propionibacterium

•Eubacterium

•Actinomyces species

Anaerobic and microaerophilic gram positive cocci, including:

•Peptococcus species

•Peptostreptococcus species

•Microaerophilic streptococci

Clostridia: Clostridia are more resistant than most anaerobes to clindamycin.

Most Clostridium perfringens are susceptible, but other species, e.g., Clostridium sporogenes and

Most Clostridium perfringens are susceptible, but other species, e.g., Clostridium sporogenes and

Clostridium tertium are frequently resistant to clindamycin. Susceptibility testing should be done.

Cross resistance has been demonstrated between clindamycin and lincomycin.

Antagonism has been demonstrated between clindamycin and erythromycin.

Human Pharmacology

Blood level studies comparing clindamycin palmitate HCl with clindamycin hydrochloride show that both drugs reach their peak active serum levels at the same time, indicating a rapid hydrolysis of the palmitate to the clindamycin.

Clindamycin is widely distributed in body fluids and tissues (including bones). Approximately 10% of the biological activity is excreted in the urine. The average serum half-life after doses of clindamycin palmitate HCl is approximately two hours in pediatric patients.

Serum half-life of clindamycin is increased slightly in patients with markedly reduced renal function. Hemodialysis and peritoneal dialysis are not effecting in removing clindamycin from the serum.

Serum level studies with clindamycin palmitate HCl in normal pediatric patients weighing 50 to 100 lbs given 2, 3 or 4 mg/kg every 6 hours (8, 12 or 16 mg/kg/day) demonstrated mean peak clindamycin serum levels of 1.24, 2.25 and 2.44 mcg/mL respectively, one hour after the first dose. By the fifth dose, the 6-hour serum concentration had reached equilibrium. Peak serum concentrations after this time would be about 2.46, 2.98 and 3.79 mcg/mL with doses of 8, 12 and 16 mg/kg/day, respectively.

Serum levels have been uniform and predictable from person to person and dose to dose. Multiple-dose studies in neonates and infants up to 6 months of age show that the drug does not accumulate in the serum and is excreted rapidly. Serum levels exceed the MICs for most indicated organisms for at least six hours following administration of the usually recommended doses of clindamycin palmitate HCl in adults and pediatric patients.

No significant levels of clindamycin are attained in the cerebrospinal fluid, even in the presence of inflamed meninges.

Pharmacokinetic studies in elderly volunteers (61 to 79 years) and younger adults (18 to 39 years) indicate that age alone does not alter clindamycin pharmacokinetics (clearance, elimination half-life, volume of distribution, and area under the serum concentration-time curve) after IV administration of clindamycin phosphate.

After oral administration of clindamycin hydrochloride, elimination half-life is increased to approximately 4.0 hours (range 3.4 to 5.1 h) in the elderly compared to 3.2 hours (range 2.1 to 4.2 h) in younger adults; administration of clindamycin palmitate HCl resulted in a similar elimination half-life value of about 4.5 hours in elderly subjects. However, the extent of absorption is not different between age groups and no dosage alteration is necessary for the elderly with normal hepatic function and normal (age-adjusted) renal function.

INDICATIONS AND USAGE

Clindamycin palmitate HCl for oral solution, USP (pediatric) is indicated in the treatment of serious infections cause by susceptible anaerobic bacteria.

Clindamycin is also indicated in the treatment of serious infections due to susceptible strains of streptococci, pneumococci and staphylococci. Its use should be reserved for penicillin-allergic patients or other patients for whom, in the judgment of the physician, a penicillin is inappropriate. Because of the risk of colitis, as described in the WARNING box, before selecting clindamycin the physician should consider the nature of the infection and the suitability of less toxic alternatives (e.g., erythromycin).

Anaerobes: Serious respiratory tract infections such as empyema, anaerobic pneumonitis and lung abscess; serious skin and soft tissue infections; septicemia; intra-abdominal infections such as peritonitis and intra-abdominal abscess (typically resulting from anaerobic organisms resident in the normal gastrointestinal tract); infections of the female pelvis and genital tract such as endometritis, nongonococcal tubo-ovarian abscess, pelvic cellulitis and postsurgical vaginal cuff infection.

Streptococci: Serious respiratory tract infections; serious skin and soft tissue infections.

Staphylococci: Serious respiratory tract infections; serious skin and soft tissue infections.

Pneumococci: Serious respiratory tract infections.

Bacteriologic studies should be performed to determine the causative organisms and their susceptibility to clindamycin.

In Vitro Susceptibility Testing

A standardized disk testing procedure is recommended for determining susceptibility of aerobic bacteria to clindamycin. A description is contained in the clindamycin palmitate HCl susceptibility disk insert. Using this method, the laboratory can designate isolates as resistant, intermediate, or susceptible.

Tube or agar dilution methods may be used for both anaerobic and aerobic bacteria. When the directions in the clindamycin palmitate HCl susceptibility powder insert are followed, an MIC (minimal inhibitory concentration) of 1.6 mcg/mL may be considered susceptible; MICs of 1.6 to 4.8 mcg/mL may be considered intermediate and MICs greater than 4.8 mcg/mL may be considered resistant.

Clindamycin palmitate HCl susceptibility disks 2 mcg. See package insert for use.

Clindamycin palmitate HCl susceptibility powder 20 mg. See package insert for use.

For anaerobic bacteria the minimal inhibitory concentration (MIC) of clindamycin can be determined by agar dilution and broth dilution (including microdilution) techniques. If MICs are not determined routinely, the disk broth method is recommended for routine use. THE KIRBY-BAUER DISK

DIFFUSION METHOD AND ITS INTERPRETIVE STANDARDS ARE NOT RECOMMENDED FOR ANAEROBES.

To reduce the development of drug-resistant bacteria and maintain the effectiveness of clindamycin palmitate HCl for oral solution, USP (pediatric) and other antibacterial drugs, clindamycin palmitate HCl for oral solution, USP (pediatric) should be used only to treat or prevent infections that are proven or strongly suspected to be caused by susceptible bacteria. When culture and susceptibility information are available, they should be considered in selecting or modifying antibacterial therapy. In the absence of such data, local epidemiology and susceptibility patterns may contribute to the empiric selection of therapy.

CONTRAINDICATIONS

This drug is contraindicated in individuals with a history of hypersensitivity to preparations containing clindamycin or lincomycin.

WARNINGS

See WARNING box.

Clostridium difficile associated diarrhea (CDAD) has been reported with use of nearly all antibacterial agents, including clindamycin palmitate HCl, and may range in severity from mild diarrhea to fatal colitis. Treatment with antibacterial agents alters the normal flora of the colon leading to overgrowth of C. difficile.

C. difficile produces toxins A and B which contribute to the development of CDAD. Hypertoxin producing strains of C. difficile cause increased morbidity and mortality, as these infections can be refractory to antimicrobial therapy and may require colectomy. CDAD must be considered in all patients who present with diarrhea following antibiotic use. Careful medical history is necessary since CDAD has been reported to occur over two months after the administration of antibacterial agents.

If CDAD is suspected or confirmed, ongoing antibiotic use not directed against C. difficile may need to be discontinued. Appropriate fluid and electrolyte management, protein supplementation, antibiotic treatment of C. difficile, and surgical evaluation should be instituted as clinically indicated.

A careful inquiry should be made concerning previous sensitivities to drugs and other allergens.

Usage in Meningitis: Since clindamycin does not diffuse adequately into the cerebrospinal fluid, the drug should not be used in the treatment of meningitis.

PRECAUTIONS

General

Review of experience to date suggests that a subgroup of older patients with associated severe illness may tolerate diarrhea less well. When clindamycin is indicated in these patients, they should be carefully monitored for change in bowel frequency.

Clindamycin palmitate HCl should be prescribed with caution in individuals with a history of gastrointestinal disease, particularly colitis.

Clindamycin palmitate HCl should be prescribed with caution in atopic individuals.

Indicated surgical procedures should be performed in conjunction with antibiotic therapy.

The use of clindamycin palmitate HCl occasionally results in overgrowth of non-susceptible organisms particularly yeasts. Should superinfections occur, appropriate measures should be taken as indicated by the clinical situation.

Clindamycin dosage modification may not be necessary in patients with renal disease. In patients with moderate to severe liver disease, prolongation of clindamycin half-life has been found. However, it was postulated from studies that when given every eight hours, accumulation should rarely occur.

Therefore, dosage modification in patients with liver disease may not be necessary. However, periodic liver enzyme determinations should be made when treating patients with severe liver disease.

Prescribing clindamycin palmitate HCl in the absence of a proven or strongly suspected bacterial infection or a prophylactic indication is unlikely to provide benefit to the patient and increases the risk of the development of drug-resistant bacteria.

Information for Patients

Patients should be counseled that antibacterial drugs including clindamycin palmitate HCl should only be used to treat bacterial infections. They do not treat viral infections (e.g., the common cold). When clindamycin palmitate HCl is prescribed to treat a bacterial infection, patients should be told that although it is common to feel better early in the course of therapy, the medication should be taken exactly as directed. Skipping doses or not completing the full course of therapy may (1) decrease the effectiveness of the immediate treatment and (2) increase the likelihood that bacteria will develop resistance and will not be treatable by clindamycin palmitate HCl or other antibacterial drugs in the future.

Diarrhea is a common problem caused by antibiotics which usually ends when the antibiotic is discontinued. Sometimes after starting treatment with antibiotics, patients can develop watery and bloody stools (with or without stomach cramps and fever) even as late as two or more months after having taken the last dose of the antibiotic. If this occurs, patients should contact their physician as soon as possible.

Laboratory Tests

During prolonged therapy, periodic liver and kidney function tests and blood counts should be performed.

Drug Interactions

Clindamycin has been shown to have neuromuscular blocking properties that may enhance the action of other neuromuscular blocking agents. Therefore, it should be used with caution in patients receiving such agents.

Antagonism has been demonstrated between clindamycin and erythromycin in vitro. Because of possible clinical significance, these two drugs should not be administered concurrently.

Carcinogenesis, Mutagenesis, Impairment of Fertility

Long term studies in animals have not been performed with clindamycin to evaluate carcinogenic potential. Genotoxicity tests performed included a rat micronucleus test and an Ames Salmonella reversion test. Both tests were negative.

Fertility studies in rats treated orally with up to 300mg/kg/day (approximately 1.6 times the highest recommended adult human oral dose based on mg/m²) revealed no effects on fertility or mating ability.

Pregnancy:

Teratogenic Effects

Pregnancy Category B

Reproduction studies performed in rats and mice using oral doses of clindamycin up to 600mg/kg/day (3.2 and 1.6 times the highest recommended adult human oral dose based on mg/m², respectively) or subcutaneous doses of clindamycin up to 250mg/kg/day (1.3 and 0.7 times the highest recommended adult human oral dose based on mg/ m², respectively) revealed no evidence of teratogenicity.

There are, however, no adequate and well-controlled studies in pregnant women. Because animal reproduction studies are not always predictive of the human response, this drug should be used during pregnancy only if clearly needed.

Nursing Mothers

Clindamycin has been reported to appear in breast milk in the range of 0.7 to 3.8 mcg/mL.

Pediatric Use

When clindamycin palmitate HCl is administered to the pediatric population (birth to 16 years), appropriate monitoring of organ system functions is desirable.

Geriatric Use

Clinical studies of clindamycin did not include sufficient numbers of patients age 65 and over to determine whether they respond differently from younger patients. However, other reported clinical experience indicates that antibiotic-associated colitis and diarrhea (due to Clostridium difficile) seen in association with most antibiotics occur more frequently in the elderly (>60 years) and may be more sever. These patients should be carefully monitored for the development of diarrhea.

Pharmacokinetic studies with clindamycin have shown no clinically important differences between young subjects (18 to 39 years) and elderly subjects (61 to 79 years) with normal hepatic function and normal (age-adjusted) renal function after oral or intravenous administration.

ADVERSE REACTIONS

The following reactions have been reported with the use of clindamycin.

Gastrointestinal: Abdominal pain, pseudomembranous colitis, esophagitis, nausea, vomiting and diarrhea (see WARNING box). The onset of pseudomembranous colitis symptoms may occur during or after antibacterial treatment (see WARNINGS).

Hypersensitivity Reactions:

Generalized mild to moderate morbilliform-like (maculopapular) skin rashes are the most frequently reported adverse reactions. Vesiculobullous rashes, as well as urticaria, have been observed during drug therapy. Rare instances of erythema multiforme, some resembling Stevens-Johnson syndrome, and a few cases of anaphylactoid reactions have also been reported.

Skin and Mucous Membranes: Pruritus, vaginitis, and rare instances of exfoliative dermatitis have been reported. (See Hypersensitivity Reactions.)

Liver: Jaundice and abnormalities in liver function tests have been observed during clindamycin therapy.

Renal: Although no direct relationship of clindamycin to renal damage has been established, renal dysfunction as evidenced by azotemia, oliguria, and/or proteinuria has been observed in rare instances.

Hematopoietic: Transient neutropenia (leukopenia) and eosinophilia have been reported. Reports of agranulocytosis and thrombocytopenia have been made. No direct etiologic relationship to concurrent clindamycin therapy could be made in any of the foregoing.

Musculoskeletal: Rare instances of polyarthritis have been reported.

OVERDOSAGE

Significant mortality was observed in mice at an intravenous dose of 855mg/kg and in rats at an oral subcutaneous dose of approximately 2618 mg/kg. In the mice, convulsions and depression were observed. Hemodialysis and peritoneal dialysis are not effective in removing clindamycin from the serum.

DOSAGE AND ADMINISTRATION

If significant diarrhea occurs during therapy, this antibiotic should be discontinued (see WARNING box).

Concomitant administration of food does not adversely affect the absorption of clindamycin palmitate HCl contained in clindamycin palmitate HCl for oral solution, USP (pediatric).

Serious infections: 8 to 12mg/kg/day (4 to 6 mg/lb/day) divided into 3 or 4 equal doses.

Severe infections: 13 to 16mg/kg/day (6.5 to 8 mg/lb/day) divided into 3 or 4 equal doses.

More severe infections: 17 to 25 mg/kg/day (8.5 to 12.5 mg/lb/day) divided into 3 or 4 equal doses.

In pediatric patients weighing 10 kg or less, ½ teaspoon (37.5 mg) three times a day should be considered the minimum recommended dose.

Serious infections due to anaerobic bacteria are usually treated with clindamycin injection. However, in clinically appropriate circumstances, the physician may elect to initiate treatment or continue treatment with clindamycin palmitate HCl for oral solution, USP (pediatric).

NOTE: In cases of β-hemolytic streptococcal infections, treatment should be continued for at least 10 days.

Reconstitution Instructions: When reconstituted with water as follows, each 5 mL (teaspoon) of solution contains clindamycin palmitate HCl equivalent to 75 mg clindamycin.

Reconstitute bottles of 100 mL with 75 mL of water. Add a large portion of the water and shake vigorously; add the remainder of the water and shake until the solution is uniform.

Storage Conditions: Store at 20° to 25°C (68° to 77°F) [See USP Controlled Room Temperature].

Do NOT refrigerate the reconstituted solution; when chilled, the solution may thicken and be difficult to pour. The solution is stable for 2 weeks at room temperature.

HOW SUPPLIED

Clindamycin palmitate HCl for oral solution, USP (pediatric) is a white to off-white powder forming a clear colorless cherry flavored solution upon constitution with water.

When reconstituted as directed, each bottle yields 100mL of solution containing 75mg of clindamycin per 5mL (NDC 10135-569-19).

Storage Conditions: Store at 20° to 25°C (68° to 77°F) [See USP Controlled Room Temperature].

ANIMAL TOXICOLOGY

One year oral toxicity studies in Spartan Sprague-Dawley rats and beagle dogs at dose levels up to 300 mg/kg/day (approximately 1.6 and 5.4 times the highest recommended adult human oral dose based on mg/m, respectively) have shown clindamycin to be well tolerated. No appreciable difference in pathological findings has been observed between groups of animals treated with clindamycin and comparable control groups. Rats receiving clindamycin hydrochloride at 600 mg/kg/day (approximately 3.2 times the highest recommended adult human oral dose based on mg/m) for 6 months tolerated the drug well; however, dogs dosed at this level (approximately 10.8 times the highest recommended adult human oral dose based on mg/m) vomited, would not eat, and lost weight.

Rx only

References

1. Smith RB, Phillips JP: Evaluation of CLEOCIN HCl and CLEOCIN Phosphate in an Aged Population. Upjohn TR 8147-82-9122-021, December 1982.

2. Bauer AW, Kirby WMM, Sherris JC, Turck M: Antibiotic susceptibility testing by a standardized single disk method. Am J. Clin. Path., 45:493–496, 1966.

Standardized Disk Susceptibility Test, Federal Register, 37:20527-29, 1972.

Trademarks are the property of their respective owners.

Manufactured for:
Marlex Pharmaceuticals, Inc.
New Castle, DE 19720

Distributed by:
Marlex Pharmaceuticals, Inc.
New Castle, DE 19720
Rev. 08/15

PRINCIPAL DISPLAY PANEL

NDC 10135-0569-19
Clindamycin
Palmitate
Hydrochloride
for Oral Solution,
USP (Pediatric)
75 mg* / 5 mL